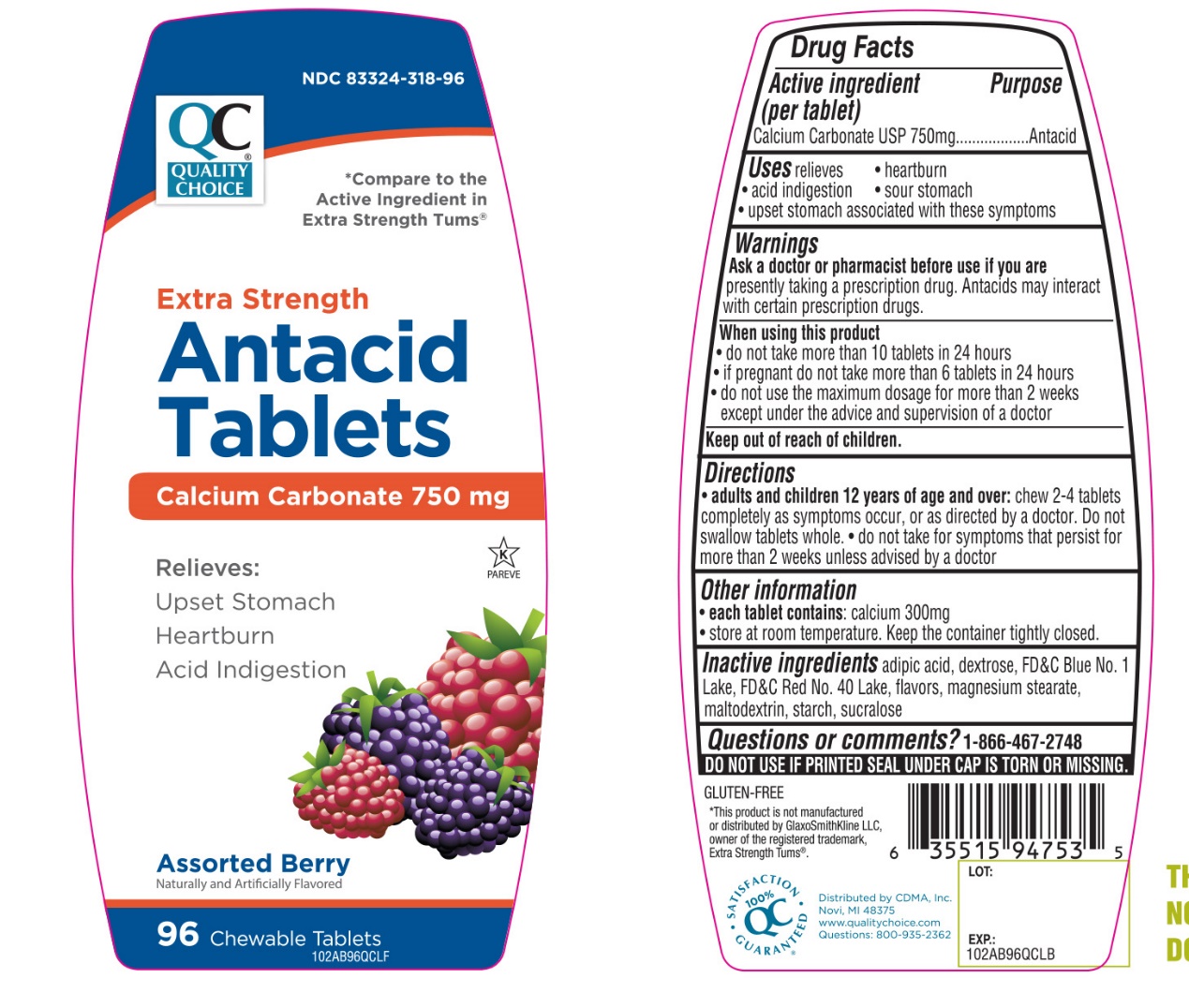 DRUG LABEL: QUALITY CHOICE

NDC: 83324-318 | Form: TABLET, CHEWABLE
Manufacturer: QUALITY CHOICE (Chain drug Marketing Assoiciation)
Category: otc | Type: HUMAN OTC DRUG LABEL
Date: 20251204

ACTIVE INGREDIENTS: CALCIUM CARBONATE 750 mg/1 1
INACTIVE INGREDIENTS: ADIPIC ACID; DEXTROSE, UNSPECIFIED FORM; FD&C BLUE NO. 1; FD&C RED NO. 40; MAGNESIUM STEARATE; MALTODEXTRIN; STARCH, CORN; SUCRALOSE

Quality Choice Extra Strength Assorted Berry Tablets Drug Facts

Active ingredient (per tablet)

Calcium Carbonate USP 750mg

Purpose

Antacid

Uses

relieves

- heartburn
- acid indigestion
- sour stomach
- upset stomach associated with these symptoms

Warnings

Ask a doctor or pharmacist before use if you arepresently taking a prescription drug. Antacids may interact with certain prescription drugs.

When using this product

- do not take more than 10 tablets in 24 hours
- if pregnant do not take more than 6 tablets in 24 hours
- do not use the maximum dosage for more than 2 weeks except under the advice and supervision of a doctor.

Directions

- adults and children 12 years of age and over:chew 2-4 tablets as symptoms occur, or as directed by a doctor
- Do not swallow tablets whole.
- do not take for symptoms that persist for more than 2 weeks unless advised by a doctor

Other information

- each tablet contains: calcium 300mg
- store at room temperature. Keep the container tightly closed.

Inactive ingredients

adipic acid, dextrose, FD&C blue #1 lake, FD&C red # 40 lake, flavors, magnesium stearate, maltodextrin, starch, sucralose.

Questions?

1-866-467-2748

Safety sealed: Do not use if printed seal under cap is torn or missing

Package/Label Principal Display Panel

NDC# 83324—318-96

*Compare to the active ingredient in Extra Strength Tums®

QUALITY CHOICE®

Extra Strength

Antacid Tablets

Calcium Carbonate 750 mg

Relieves:

- Upset Stomach
- Heartburn
- Acid indigestion

Assorted Berry

Naturally and Artificially Flavored

96 CHEWABLE TABLETS

GLUTEN- FREE

K PAREVE

100% QC SATISFACTION GUARANTEED

Distributed By:

C.D.M.A. Inc

Novi, MI 48375

www.qualitychoice.com

Questions: 800-935-2362

*This product is not manufactured or distributed by GlaxoSmithKline LLC, owner of the registered trademark, Extra Strength Tums®.